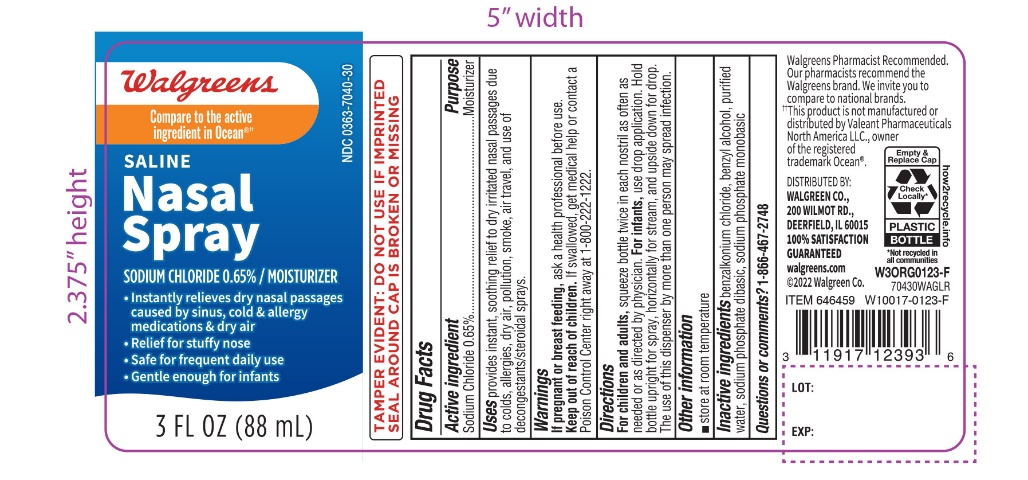 DRUG LABEL: Walgreens Saline
NDC: 0363-7040 | Form: SPRAY
Manufacturer: WALGREEN COMPANY
Category: otc | Type: HUMAN OTC DRUG LABEL
Date: 20251201

ACTIVE INGREDIENTS: SODIUM CHLORIDE 6.5 mg/1 mL
INACTIVE INGREDIENTS: BENZALKONIUM CHLORIDE; BENZYL ALCOHOL; WATER; SODIUM PHOSPHATE, DIBASIC, UNSPECIFIED FORM; SODIUM PHOSPHATE, MONOBASIC, UNSPECIFIED FORM

Walgreen Saline Nasal Spray

Active Ingredients

Sodium Chloride 0.65%

Purpose

Moisturizer

Uses

provides instant, soothing relief dry irritated nasal passages due to colds, allergies, dry air, pollution, smoke, air travel and use of decongestants/steroidal sprays.

Warnings

If pregnant or breast-feeding, ask a healthcare professional before use.

Keep out of reach of children.

If swallowed, get medical help or contact a Poison Control Center right away at 1-800-222-1222

Directions

For children and adults,squeeze bottle twice in each nostril as often as needed or as directed by physician. For infants,use drop application. Hold bottle upright for spray, horizontally for stream, and upside down for drop. The use of this dispenser by more than one person may spread infection.

Other Information

- store at room temperature

Inactive Ingredients

benzalkonium chloride, benzyl alcohol, purified water, sodium phosphate dibasic, sodium phosphate monobasic

Questions or comments?

1-866-467-2748

*This product is not manufactured or distributed by Valeant Pharmaceuticals North America LLC, owner of the registered trademark Ocean.

Saline Nasal Spray

Compare to the active ingredient in Ocean®*

Saline Nasal Spray

Sodium Chloride 0.65%

- Instantly relieves dry nasal passages caused by sinus, cold and allergy medications and dry air
- Safe for frequent daily use
- Gentle enough for infants
- Relief for stuffy noses

TAMPER EVIDENT: DO NOT USE IF IMPRINTED SEAL AROUND CAP IS BROKEN OR MISSING.

Distributed by: